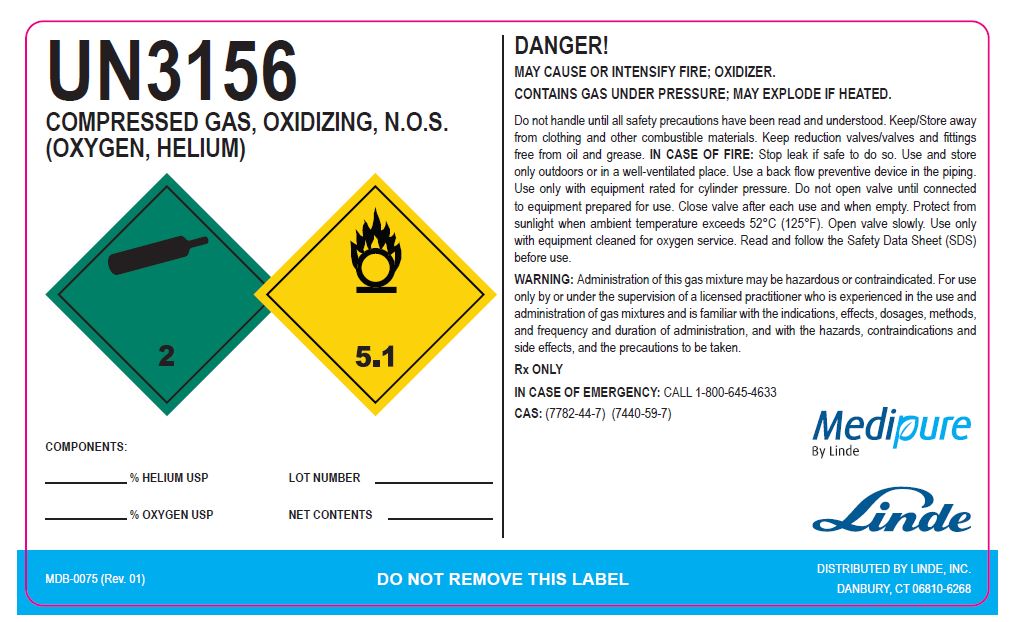 DRUG LABEL: Helium Oxygen mixture
NDC: 59579-009 | Form: GAS
Manufacturer: Linde Gas & Equipment Inc.
Category: prescription | Type: HUMAN PRESCRIPTION DRUG LABEL
Date: 20250124

ACTIVE INGREDIENTS: HELIUM 800 mL/1 L; OXYGEN 200 mL/1 L

Helium Oxygen Mixture

PACKAGE LABEL

UN3156

COMPRESSED GAS,

OXIDIZING, N.O.S.

(OXYGEN, HELIUM)

% HELIUM USP LOT NUMBER

% OXYGEN USP NET CONTENTS

DANGER!

MAY CAUSE OR INTENSIFY FIRE; OXIDIZER.

CONTAINS GAS UNDER PRESSURE; MAY EXPLODE IF HEATED

Do not handle until all safety precautions have been read and understood. Keep/Store away from clothing and other combustible materials. Keep reduction valves/valves and fittings from oil and grease. IN CASE OF FIRE: Stop leak if safe to do so. Use and store only outdoors or in a well-ventilated place. Use a back flow preventative device in the piping. Use only with equipment rated for cylinder pressure. Do not open valve until connected to equipment prepared for use. Close valve after each use and when empty. Protect from sunlight when ambient temperature exceeds 52°C (125ºF). Open valve slowly. Use only equipment cleaned for oxygen service. Read and follow the Safety Data Sheet (SDS) before use.

WARNING: Administration of this gas mixture may be hazardous or contraindicated. For use only by or under the supervision of a licensed practitioner who is experienced in the use and administration of gas mixtures and is familiar with the indications, effects, dosages, methods and frequency and duration of administration, and with the hazards, contraindications, and side effects and the precautions to be taken.

Rx only

IN CASE OF EMERGENCY CALL 1-800-645-4633

CAS: (7782-44-7) (7440-59-7)

Medipure By Linde

MDB-0075 (Rev. 01) DO NOT REMOVE THIS LABEL DISTRIBUTED BY LINDE, INC. DANBURY, CT 06810-6268